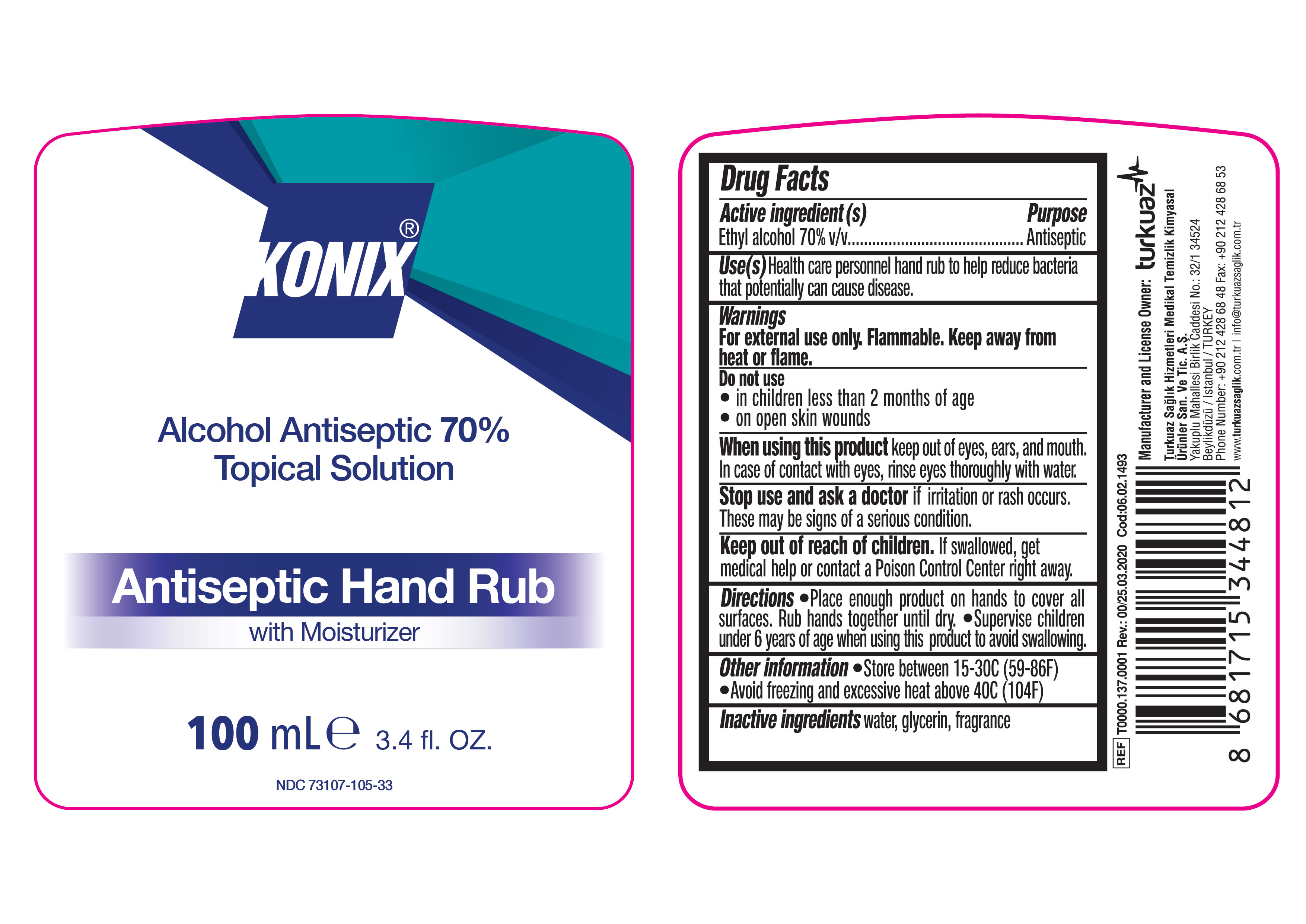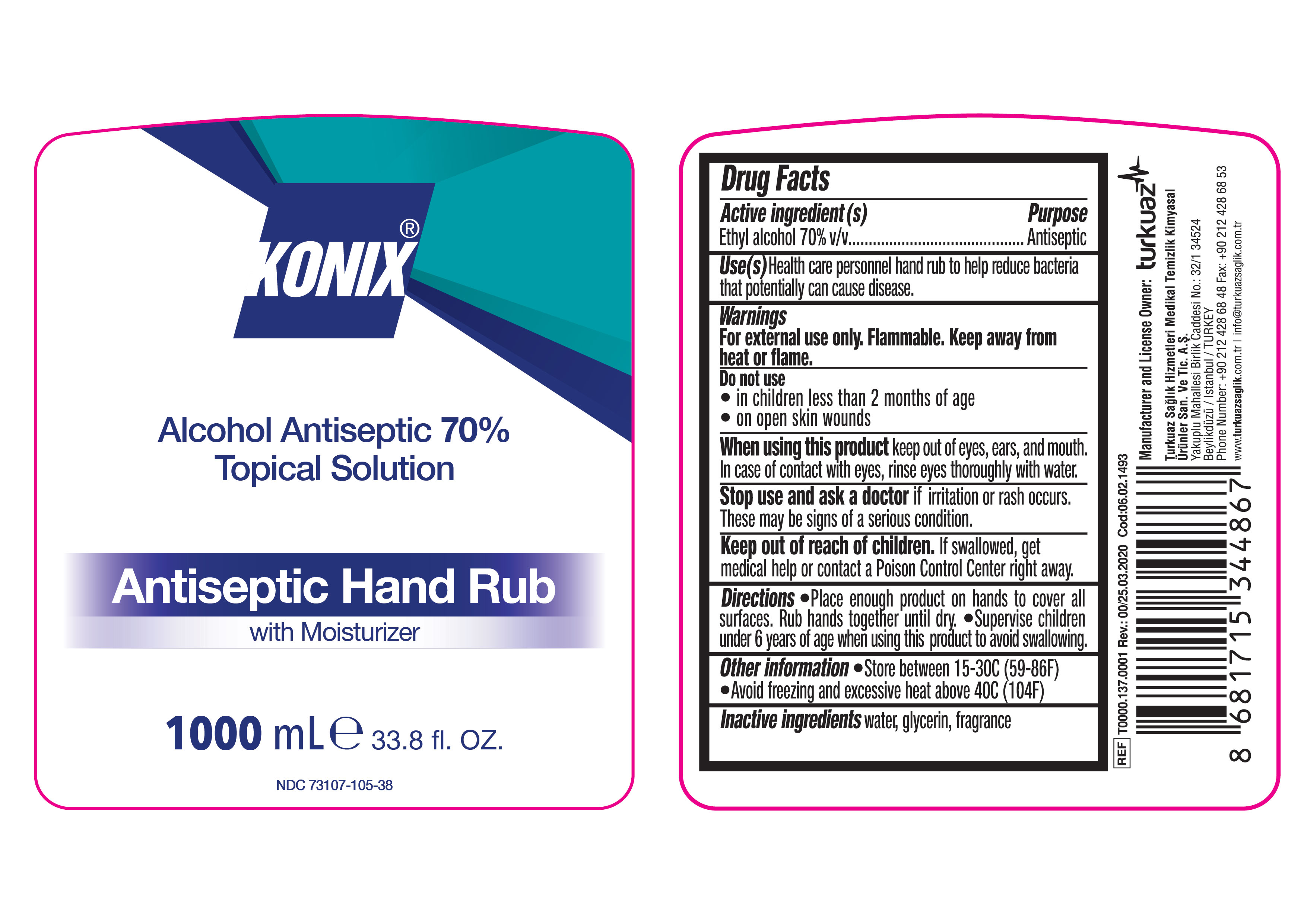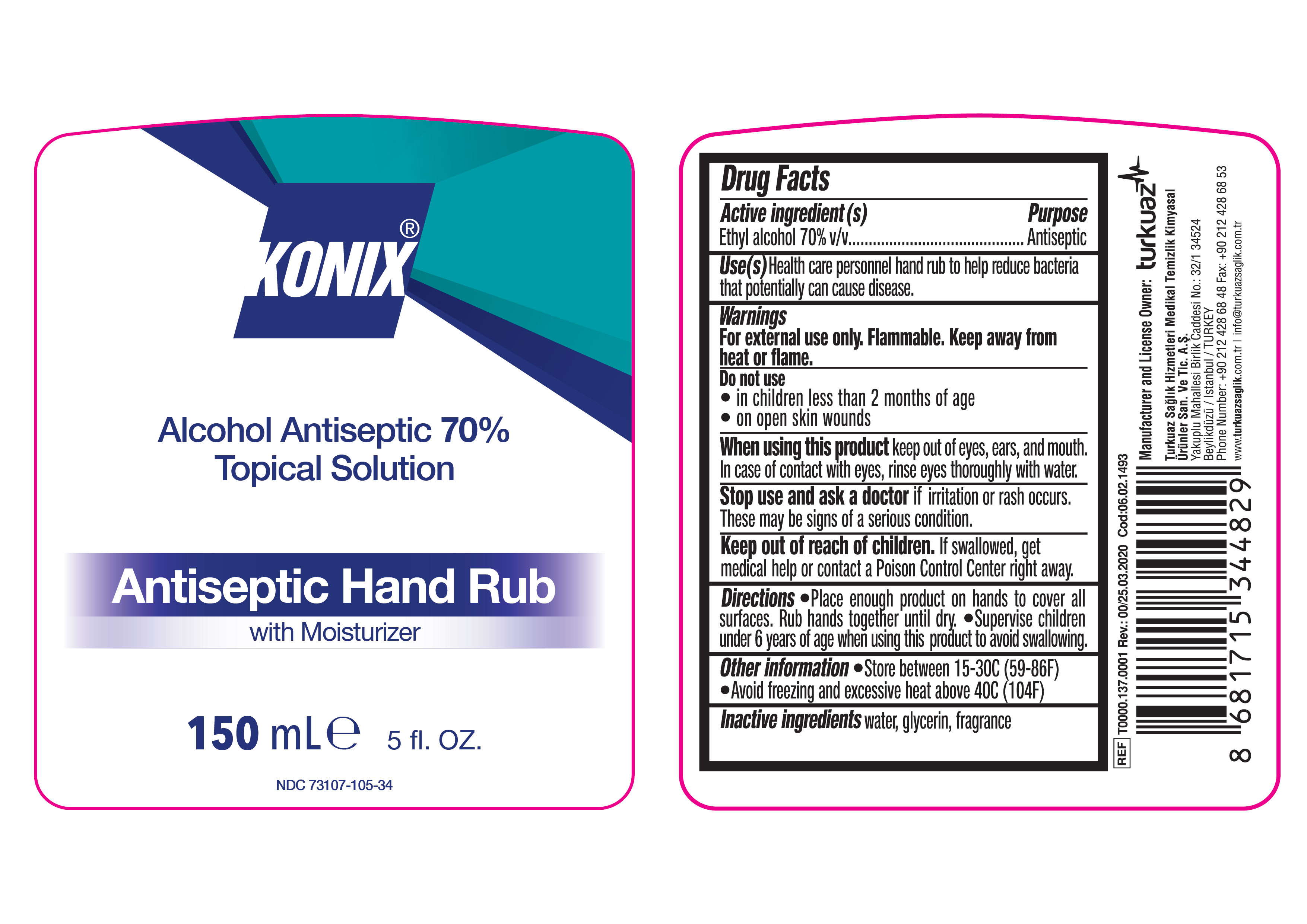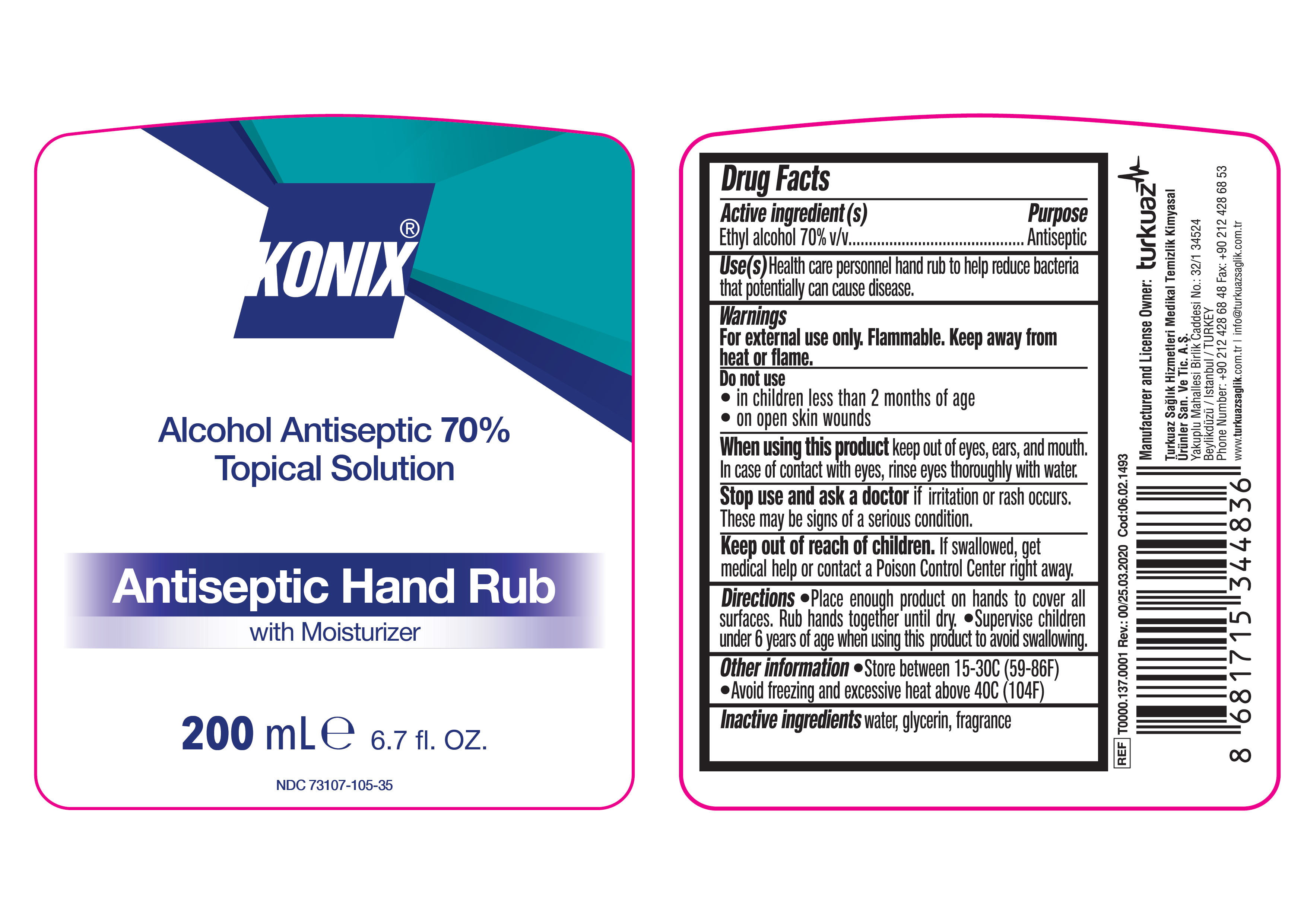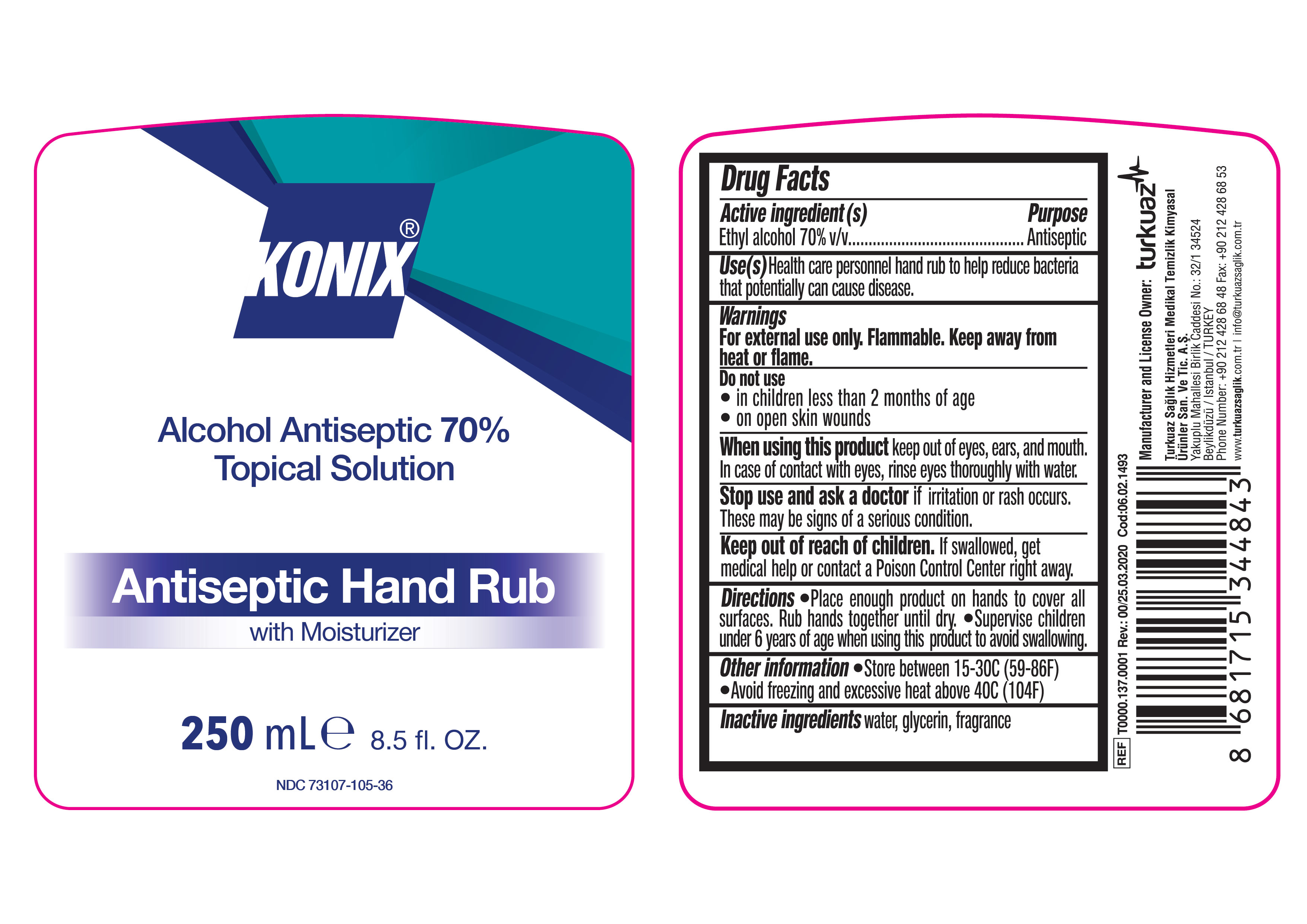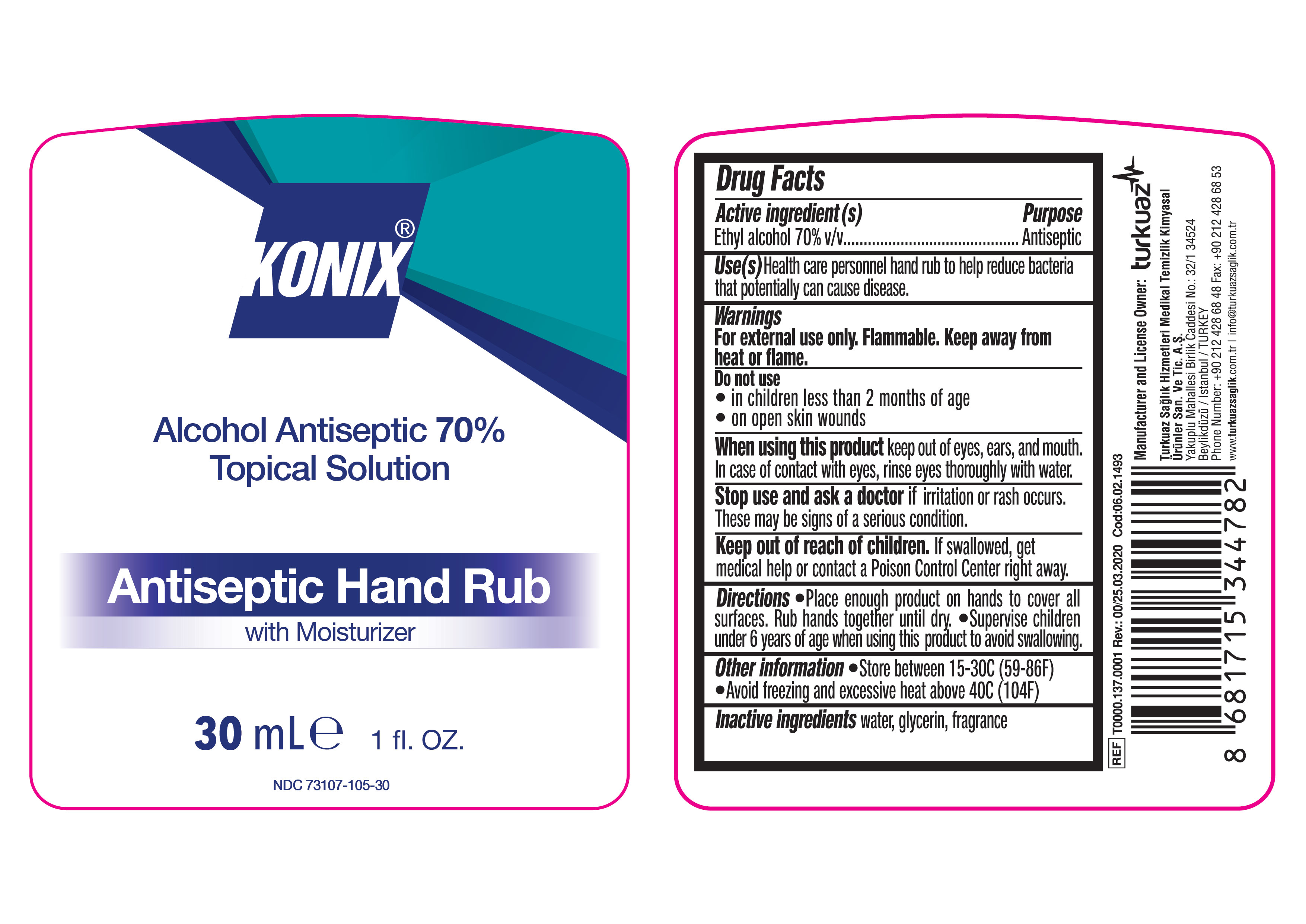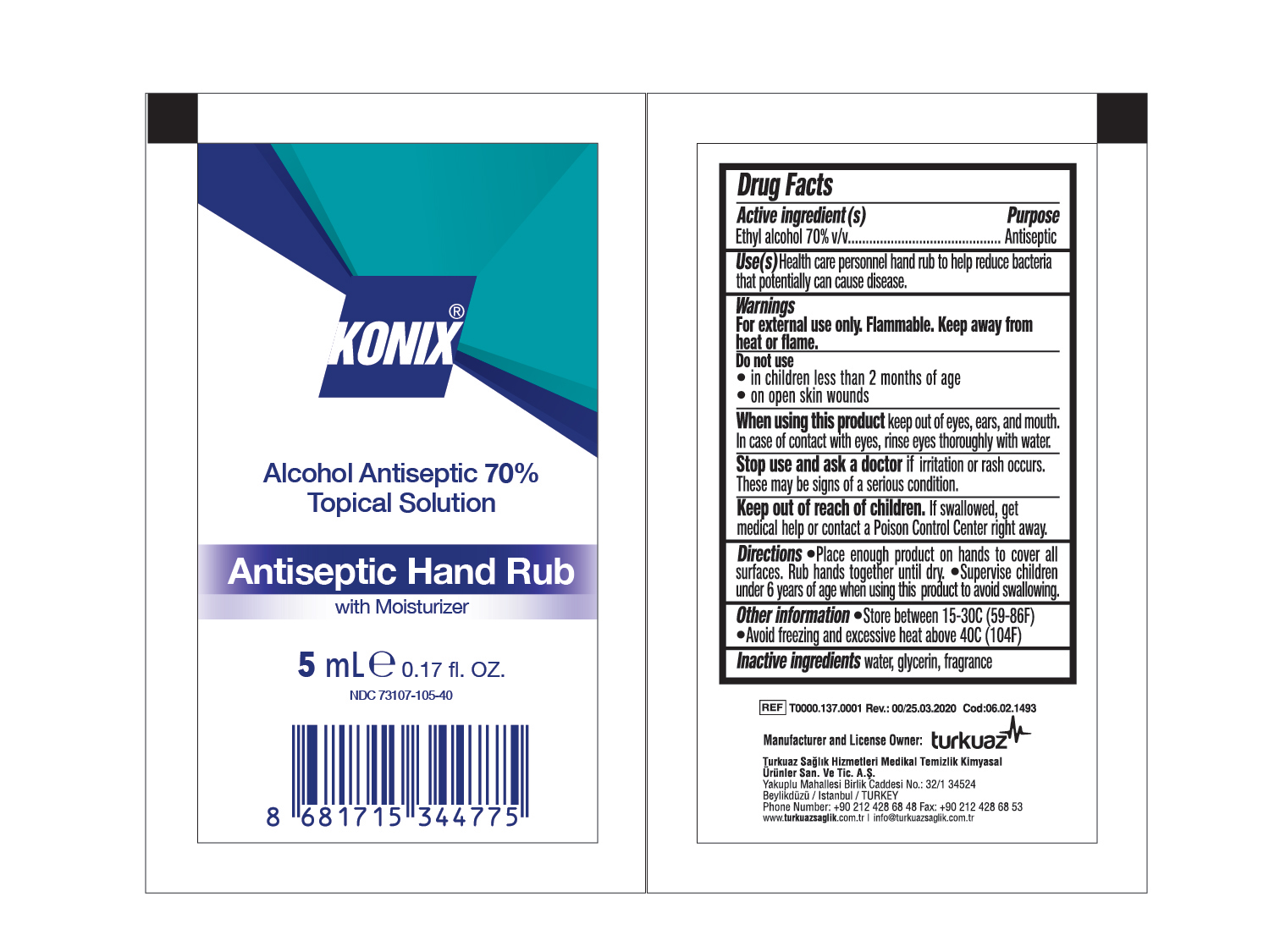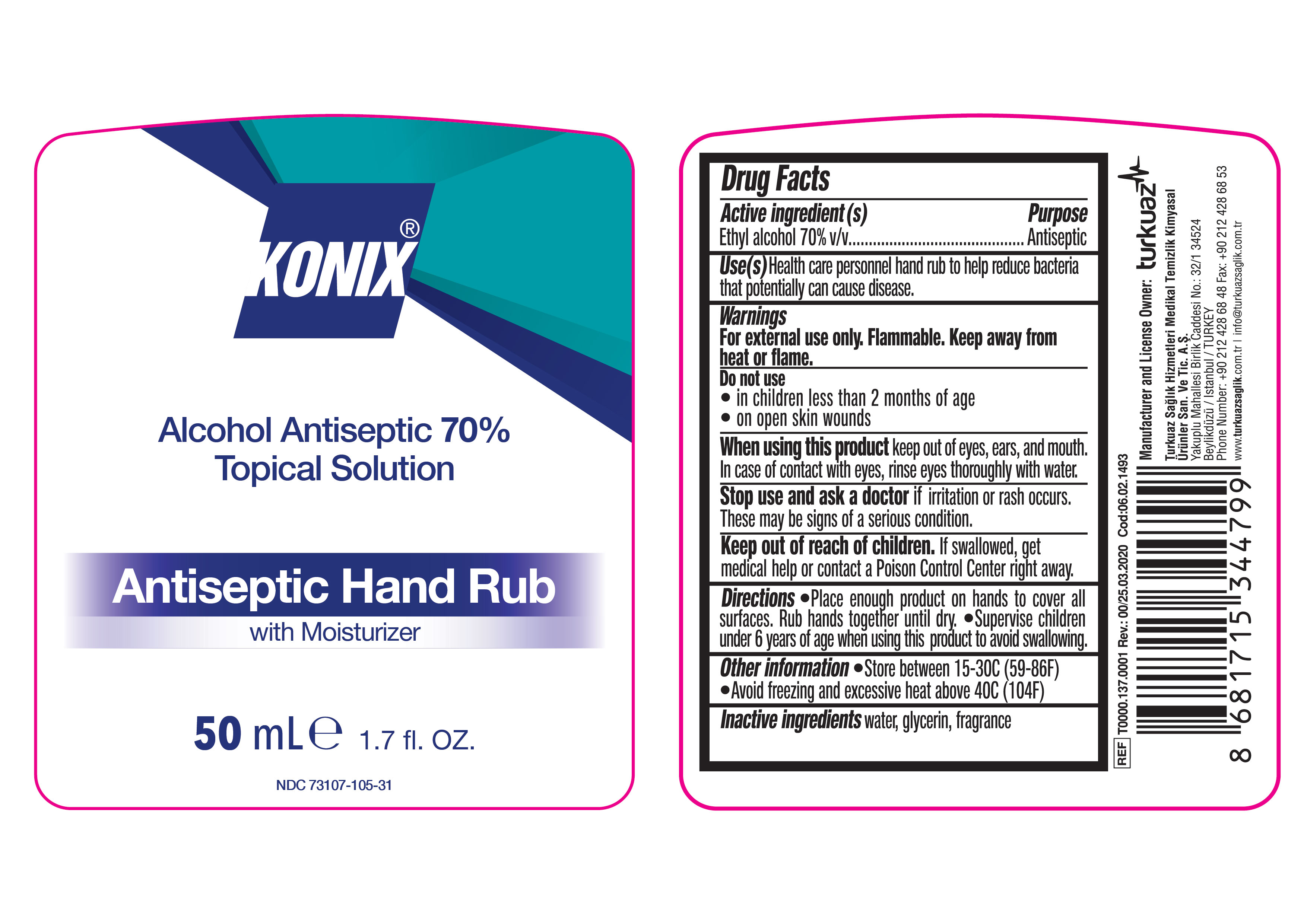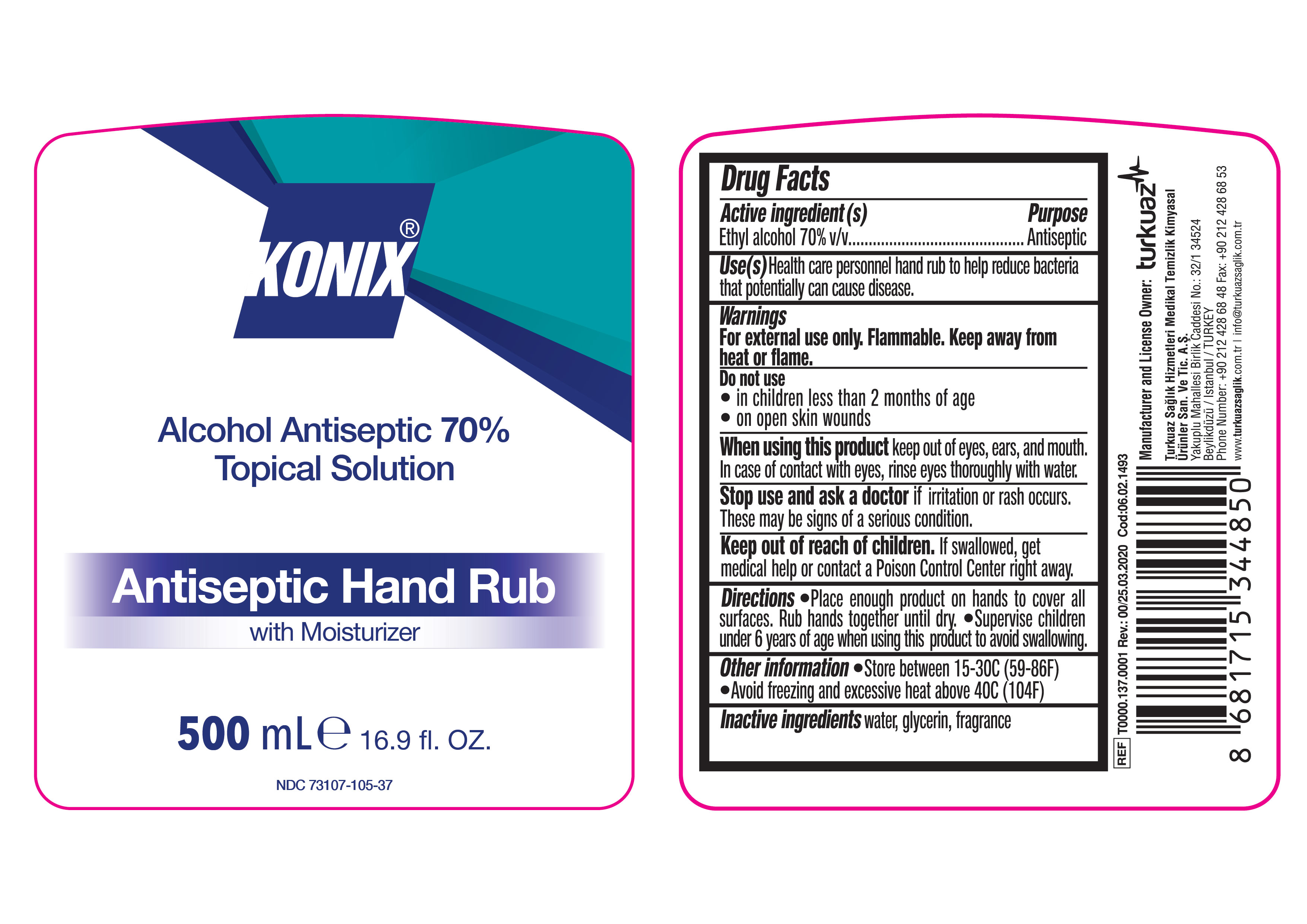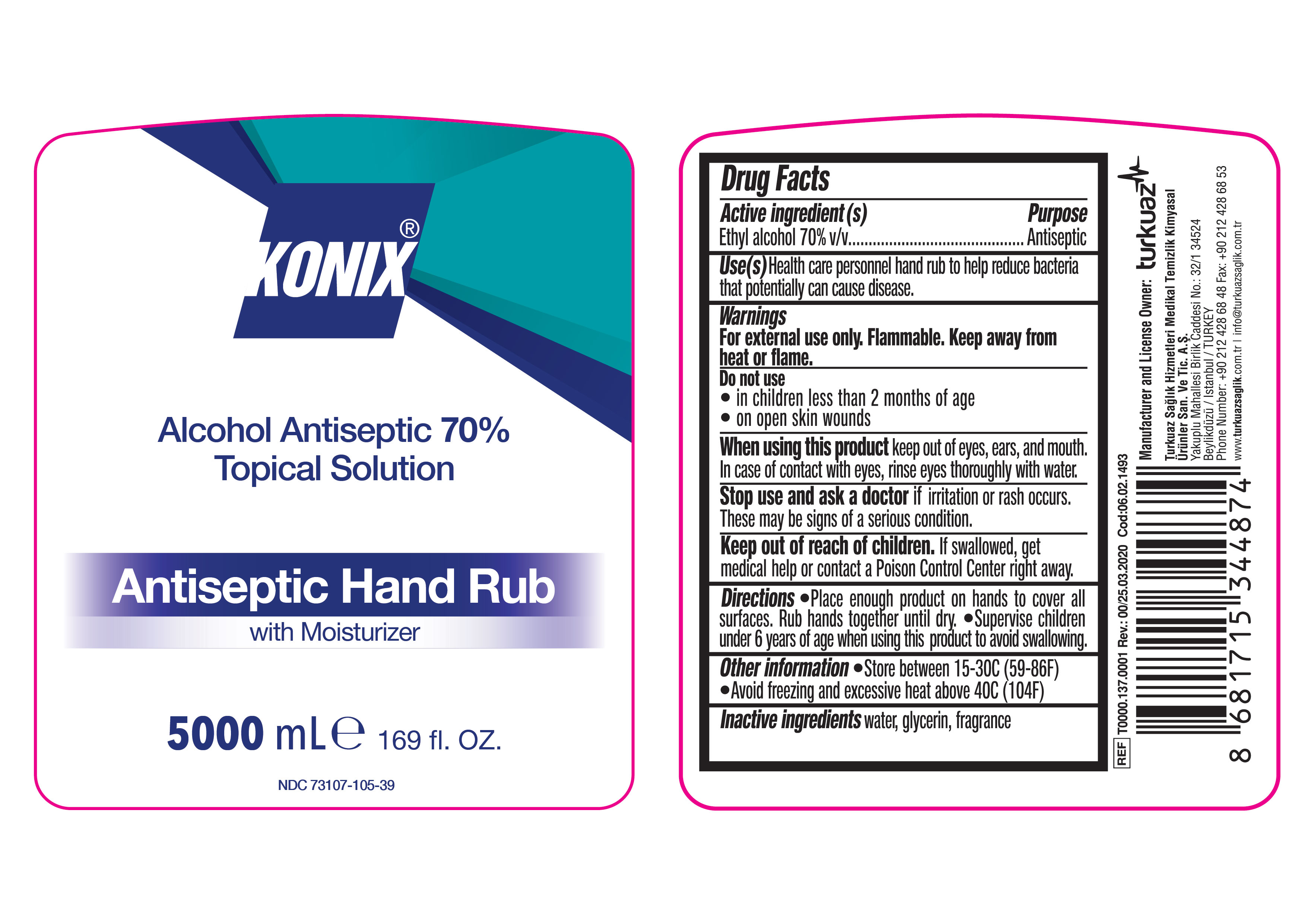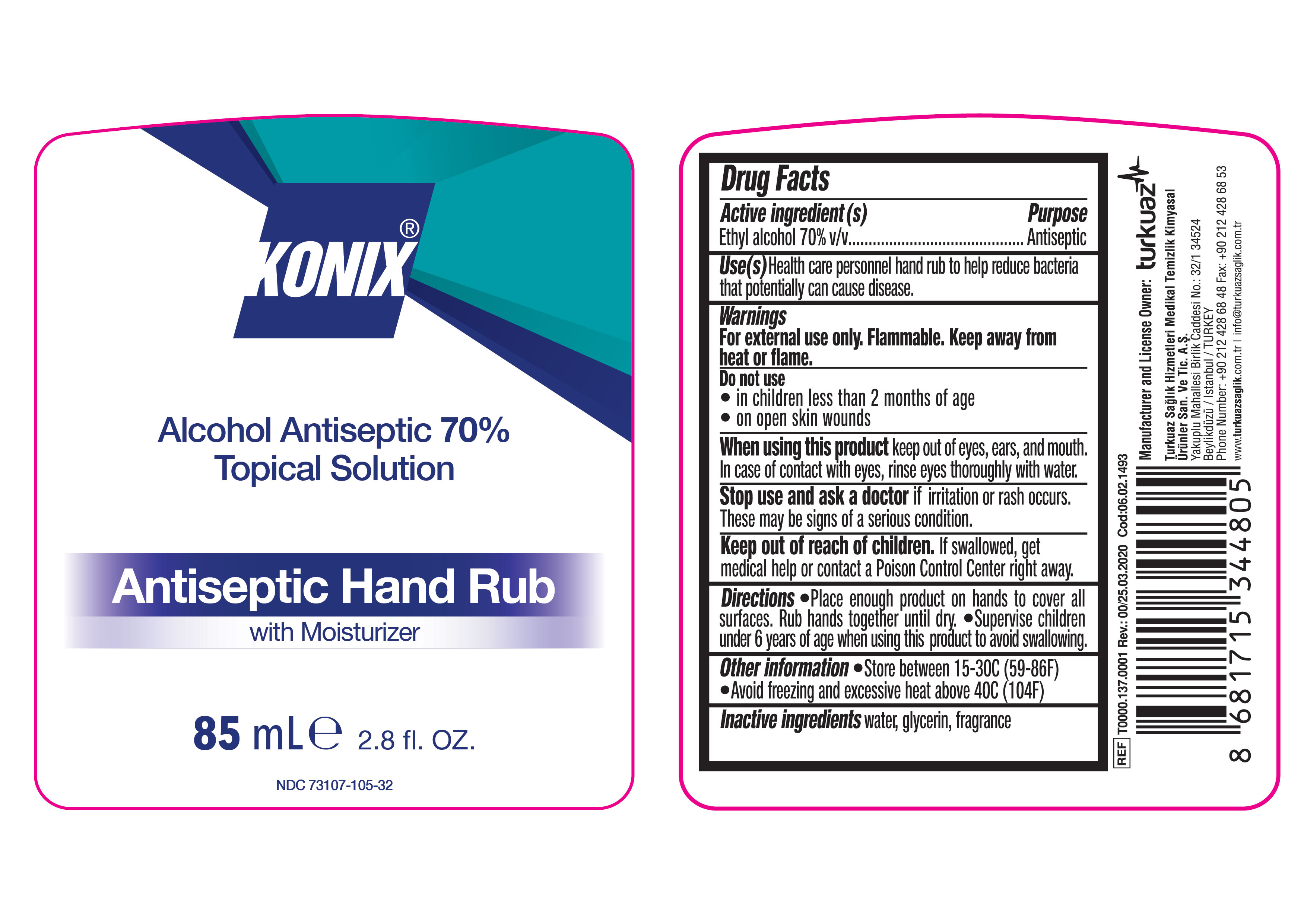 DRUG LABEL: KONIX Alcohol Antiseptic Hand Rub
NDC: 73107-105 | Form: SOLUTION
Manufacturer: TURKUAZ SAGLIK HIZMETLERI MEDIKAL TEMIZLIK KIMYASAL URUNLER SANAYI VE TICARET AS
Category: otc | Type: HUMAN OTC DRUG LABEL
Date: 20250129

ACTIVE INGREDIENTS: ALCOHOL 70 mL/100 mL
INACTIVE INGREDIENTS: WATER; GLYCERIN

KONIX Alcohol Antiseptic 70% Topical Solution Antiseptic Hand Rub with Moisturizer

Active Ingredient(s)

Alcohol 70% v/v

Purpose

Antiseptic, Hand Rub

Use

Health care personnel hand rub to help reduce bacteria that potentially can cause disease.

Warnings

For external use only. Flammable. Keep away from heat or flame.

Do not use

- in children less than 2 months of age

- on open skin wounds

When using this product keep out of eyes, ears, and mouth. In case of contact with eyes, rinse eyes thoroughly with water.

Stop use and ask a doctor if irritation or rash occurs. These may be signs of a serious condition.

Keep out of reach of children. If swallowed, get medical help or contact a Poison Control Center right away.

Directions

- Place enough product on hands to cover all surfaces. Rub hands together until dry.

- Supervise children under 6 years of age when using this product to avoid swallowing.

Other information

- Store between 15-30C (59-86F)
- Avoid freezing and excessive heat above 40C (104F)

Inactive ingredients

water, glycerin, fragrance

PACKAGE LABEL

Alcohol Antiseptic 70%

Topical Solution

Antiseptic Hand Rub with Moisturizer

5ml 0.17fl.OZ NDC: 73107-105-40

PACKAGE LABEL

Alcohol Antiseptic 70%

Topical Solution

Antiseptic Hand Rub with Moisturizer

30ml 1fl.OZ NDC: 73107-105-30

PACKAGE LABEL

Alcohol Antiseptic 70%

Topical Solution

Antiseptic Hand Rub with Moisturizer

50ml 1.7fl.OZ NDC: 73107-105-31

PACKAGE LABEL

Alcohol Antiseptic 70%

Topical Solution

Antiseptic Hand Rub with Moisturizer

85ml 2.8fl.OZ NDC: 73107-105-32

PACKAGE LABEL

Alcohol Antiseptic 70%

Topical Solution

Antiseptic Hand Rub with Moisturizer

100ml 3.4 fl.OZ NDC: 73107-105-33

PACKAGE LABEL

Alcohol Antiseptic 70%

Topical Solution

Antiseptic Hand Rub with Moisturizer

150ml 5fl.OZ NDC: 73107-105-34

>

PACKAGE LABEL

Alcohol Antiseptic 70%

Topical Solution

Antiseptic Hand Rub with Moisturizer

200ml 6.7fl.OZ NDC: 73107-105-35

PACKAGE LABEL

Alcohol Antiseptic 70%

Topical Solution

Antiseptic Hand Rub with Moisturizer

250ml 8.5fl.OZ NDC: 73107-105-36

PACKAGE LABEL

Alcohol Antiseptic 70%

Topical Solution

Antiseptic Hand Rub with Moisturizer

500ml 16.9 fl.OZ NDC: 73107-105-37

PACKAGE LABEL

Alcohol Antiseptic 70%

Topical Solution

Antiseptic Hand Rub with Moisturizer

1000ml 33.8fl.OZ NDC: 73107-105-38

PACKAGE LABEL

Alcohol Antiseptic 70%

Topical Solution

Antiseptic Hand Rub with Moisturizer

5000ml 169fl.OZ NDC: 73107-105-39